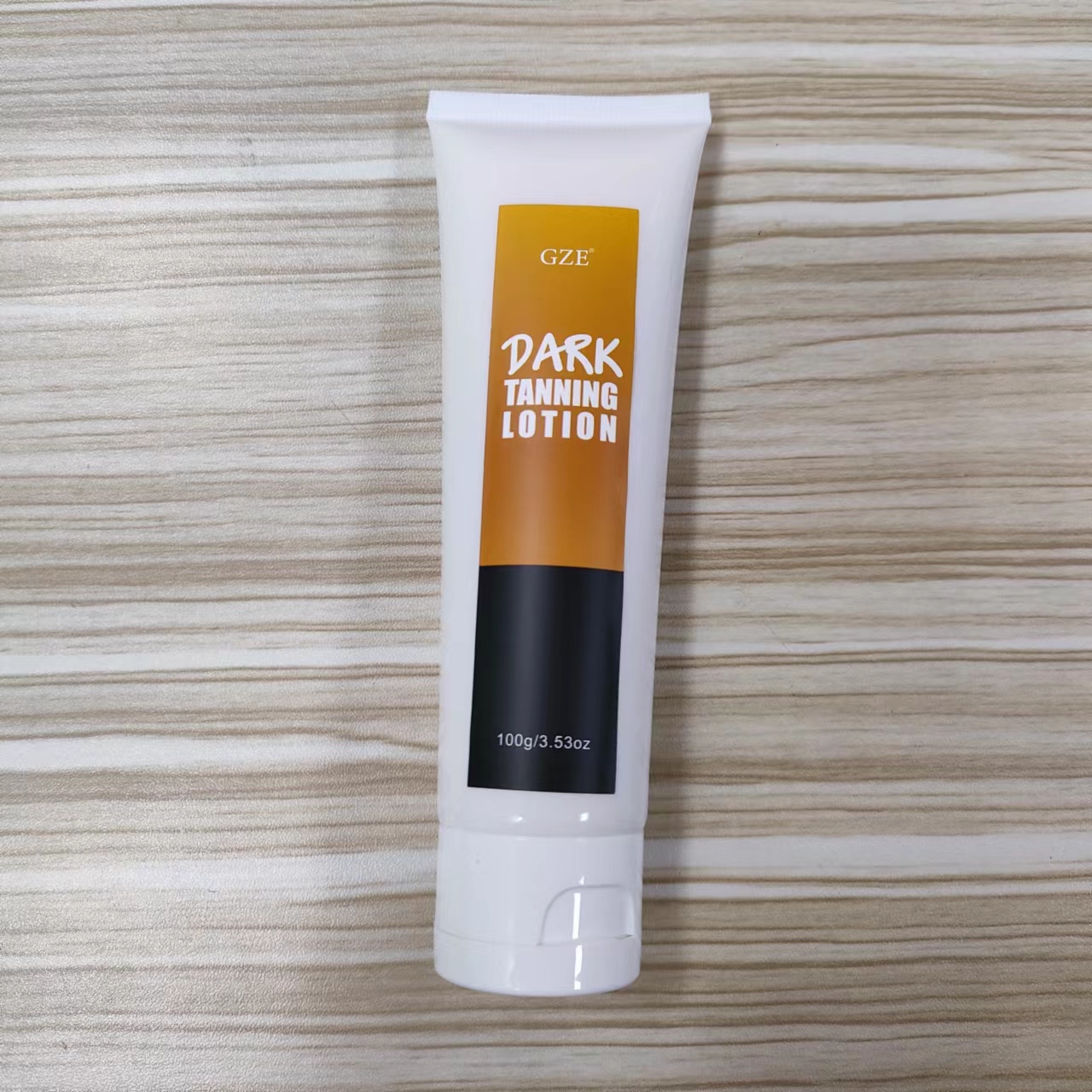 DRUG LABEL: GZE Dark TanningLotion
NDC: 74458-294 | Form: LOTION
Manufacturer: Guangzhou Yilong Cosmetics Co.,Ltd.
Category: otc | Type: HUMAN OTC DRUG LABEL
Date: 20241028

ACTIVE INGREDIENTS: ALOE BARBADENSIS LEAF JUICE 10 g/100 g
INACTIVE INGREDIENTS: RETINYL PALMITATE; PEG-100 STEARATE; GLYCERIN; CARAMEL; CITRIC ACID MONOHYDRATE; .ALPHA.-TOCOPHEROL ACETATE; AQUA

GZE DARK TANNING LOTION

ACTIVE INGREDIENT

Retinyl Palmitate

INACTIVE INGREDIENT

Aqua, Glycerin, PEG-100 Stearate, Caramel, Fragrance, Tocopheryl Acetate, Citric Acid, Aloe Barbadensis Leaf Juice.

PURPOSE

Evenly brightens skin tone.

INDICATIONS AND USAGE

Apply a generous amount of tanning lotion to clean, dry skin. Rub in completely and evenly, making sure to cover all areas. Wait for the lotion to fully absorb before dressing. Reapply as necessary for desired results.

WARNINGS

For external use only.

Stop use and ask a doctor if rash occurs.

Do not use on damaged or broken skin.

When using this product keep out of eyes. Rinse with water to remove.

Keep out of reach of children. If swallowed, get medical help or contact a Poison Control Center right away.

DOSAGE AND ADMINISTRATION

Apply a generous amount of tanning lotion to clean, dry skin. Rub in completely and evenly, making sure to cover all areas. Wait for the lotion to fully absorb before dressing. Reapply as necessary for desired results.